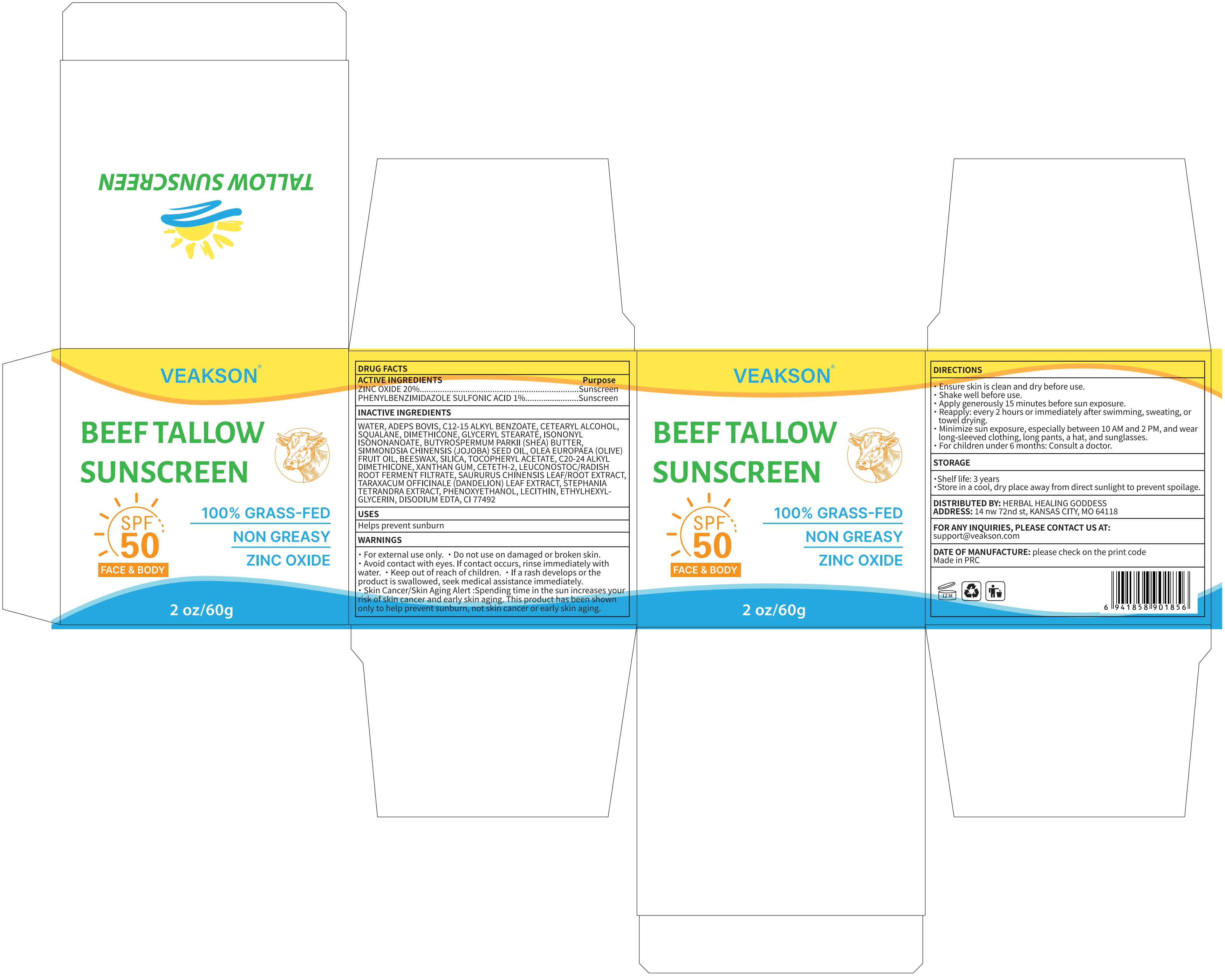 DRUG LABEL: VEAKSON BEEF TALLOW SUNSCREEN
NDC: 83566-563 | Form: CREAM
Manufacturer: Guangdong Aimu Biological Technology Co., Ltd
Category: otc | Type: HUMAN OTC DRUG LABEL
Date: 20260104

ACTIVE INGREDIENTS: ZINC OXIDE 20 g/100 g; PHENYLBENZIMIDAZOLE SULFONIC ACID 1 g/100 g
INACTIVE INGREDIENTS: CETEARYL ALCOHOL; STEPHANIA TETRANDRA WHOLE; PHENOXYETHANOL; ETHYLHEXYLGLYCERIN; ALPHA-TOCOPHEROL ACETATE; CI 77492; CETETH-2; SAURURUS CHINENSIS WHOLE; C12-15 ALKYL BENZOATE; LEUCONOSTOC/RADISH ROOT FERMENT FILTRATE; SILICA; SIMMONDSIA CHINENSIS (JOJOBA) SEED OIL; DIMETHICONE; SOYBEAN LECITHIN; ETHYLHEXYL SALICYLATE; OLEA EUROPAEA (OLIVE) FRUIT OIL; BEESWAX; ISONONYL ISONONANOATE; SQUALANE; BUTYROSPERMUM PARKII (SHEA) BUTTER; GLYCERYL STEARATE; EDETATE DISODIUM; XANTHAN GUM; WATER; TARAXACUM OFFICINALE (DANDELION) ROOT; ADEPS BOVIS

VEAKSON BEEF TALLOW SUNSCREEN

Active Ingredients

ZINC OXIDE 20%
PHENYLBENZIMIDAZOLE SULFONIC ACID 1%

Purpose

Sunscreen

Uses

Ensure skin is clean and dry before use.

Shake well before use.
Apply generously 15 minutes before sun exposure;
Reapply: every 2 hours or immediately after swimming, sweating, or towel drying.

Minimize sun exposure, especially between 10 AM and 2 PM, and wear long-sleeved clothing, long pants, a hat, and sunglasses;
For children under 6 months: Consult a doctor.

Warnings

For external use only.

SkinCancer/SkinAging Alert :Spending time in the sun increases your risk of skin cancer and early skin aging. This product has been shown only to help prevent sunburn, notskin cancer or early skin aging.

Stop Use

If a rash develops or the product is swallowed, seek medical assistance immediately

Do not use on damaged or broken skin.

When Using

Avoid contact with eyes. If contact occurs, rinse immediately with water.

Keep Out Of Reach Of Children

If a rash develops or the product is swallowed, seek medical assistance immediately.

Inactive ingredients

WATER 31.76%
ETHYLHEXYL SALICYLATE 5%
ADEPS BOVIS 5%
C12-15 ALKYL BENZOATE 4%
CETEARYL ALCOHOL 3.5%
SQUALANE 3%
DIMETHICONE 3%
GLYCERYL STEARATE 3%
ISONONYL ISONONANOATE 3%
BUTYROSPERMUM PARKII (SHEA) BUTTER 3%
SIMMONDSIA CHINENSIS (JOJOBA) SEED OIL 3%
OLEA EUROPAEA (OLIVE) FRUIT OIL 2%
BEESWAX 2%
SILICA 2%
TOCOPHERYL ACETATE 1%
C20-24 ALKYL DIMETHICONE 1%
XANTHAN GUM 0.6%
CETETH-2 0.5%
LEUCONOSTOC/RADISH ROOT FERMENT FILTRATE 0.5%
SAURURUS CHINENSIS LEAF/ROOT EXTRACT 0.5%
TARAXACUM OFFICINALE (DANDELION) LEAF EXTRACT 0.5%
STEPHANIA TETRANDRA EXTRACT 0.5%
PHENOXYETHANOL 0.45%
LECITHIN 0.1%
ETHYLHEXYLGLYCERIN 0.05%
DISODIUM EDTA 0.02%
CI 77492 0.02%

Dosage & administration

Apply generously 15 minutes before sun exposure.